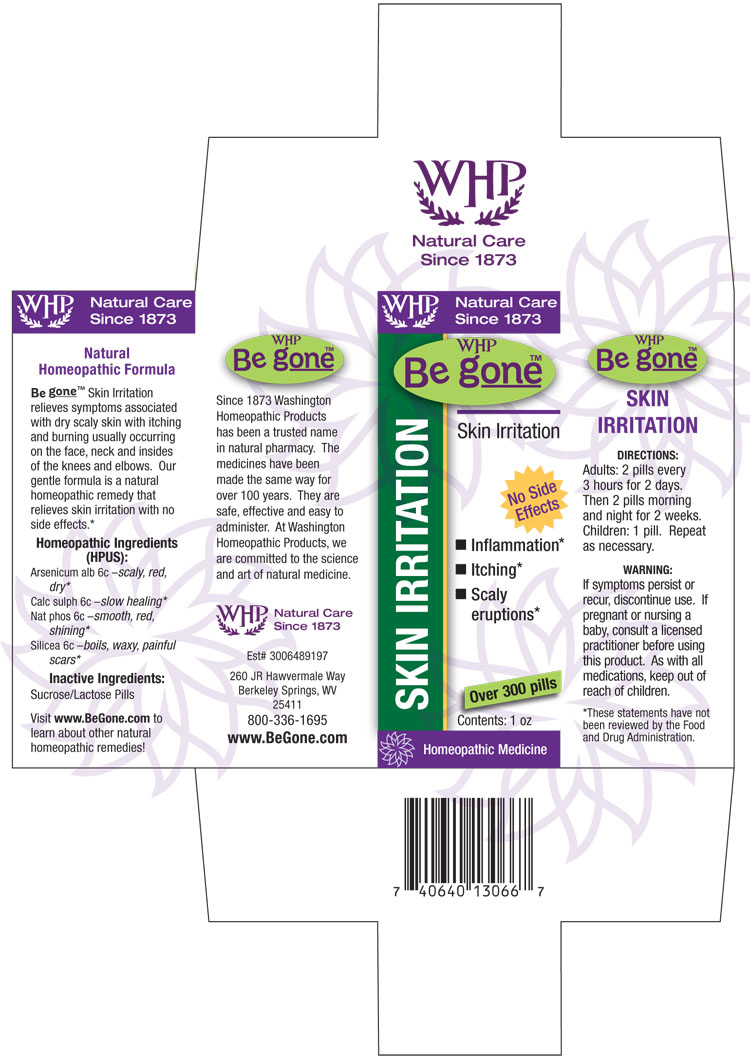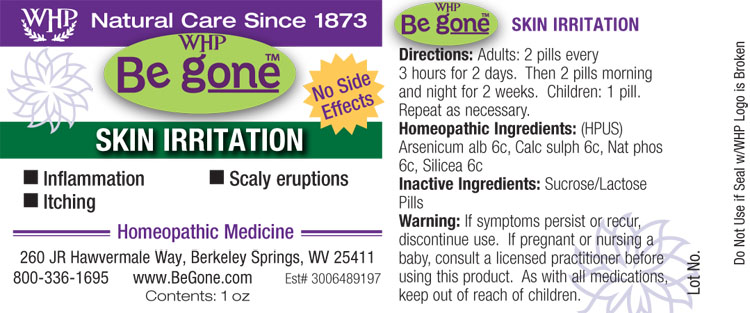 DRUG LABEL: WHP Be gone Skin Irritation
NDC: 68428-749 | Form: PELLET
Manufacturer: Washington Homeopathic Products
Category: homeopathic | Type: HUMAN OTC DRUG LABEL
Date: 20140508

ACTIVE INGREDIENTS: ARSENIC TRIOXIDE 6 [hp_C]/1 1; CALCIUM SULFATE ANHYDROUS 6 [hp_C]/1 1; SODIUM PHOSPHATE, DIBASIC, HEPTAHYDRATE 6 [hp_C]/1 1; SILICON DIOXIDE 6 [hp_C]/1 1
INACTIVE INGREDIENTS: SUCROSE; LACTOSE

DRUG FACTS

ACTIVE INGREDIENTS

ARSENICUM ALB

CALC SULPH

NAT PHOS

SILICEA

USES

Relieves symptoms associated with dry scaly skin with itching and burning usually occurring on the face, neck and insides of the knees and elbows.

KEEP OUT OF REACH OF CHILDREN

As with all medications, keep out of reach of children.

INDICATIONS

ARSENICUM ALB Scaley, red, dry

CALC SULPH Slow healing

NAT PHOS Smooth, red, shining

SILICEA Boils, waxy, painful scars

STOP USE AND ASK DOCTOR

If symptoms persist or recur, discontinue use. If pregnant or nursing a baby, consult a licensed practitioner before using this product.

DIRECTIONS

Adults: 2 pills every 3 hours for 2 days. Then 2 pills morning and night for 2 weeks.

Children: 1 pill.

Repeat as necessary.

INACTIVE INGREDIENTS

Sucrose/Lactose